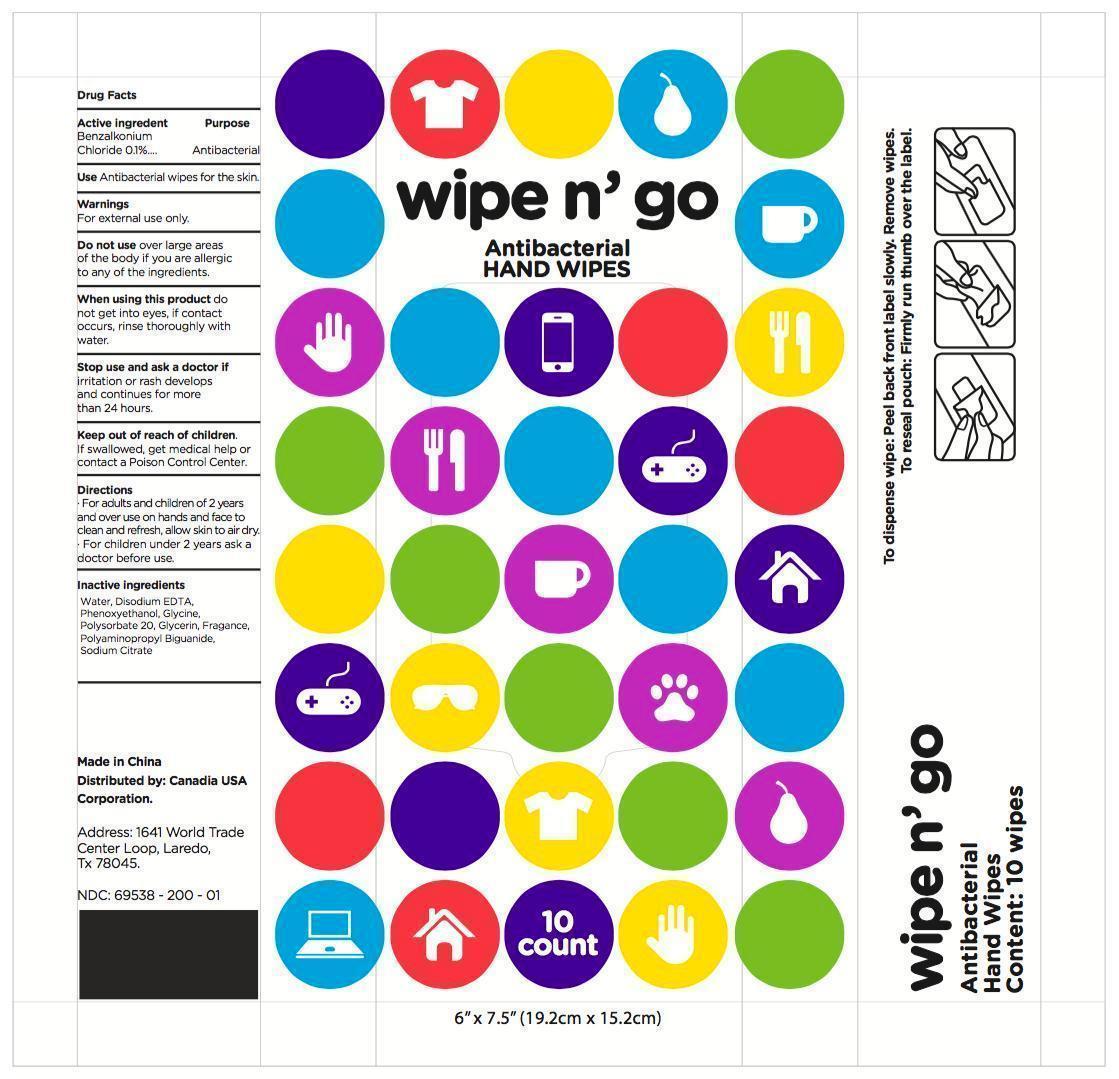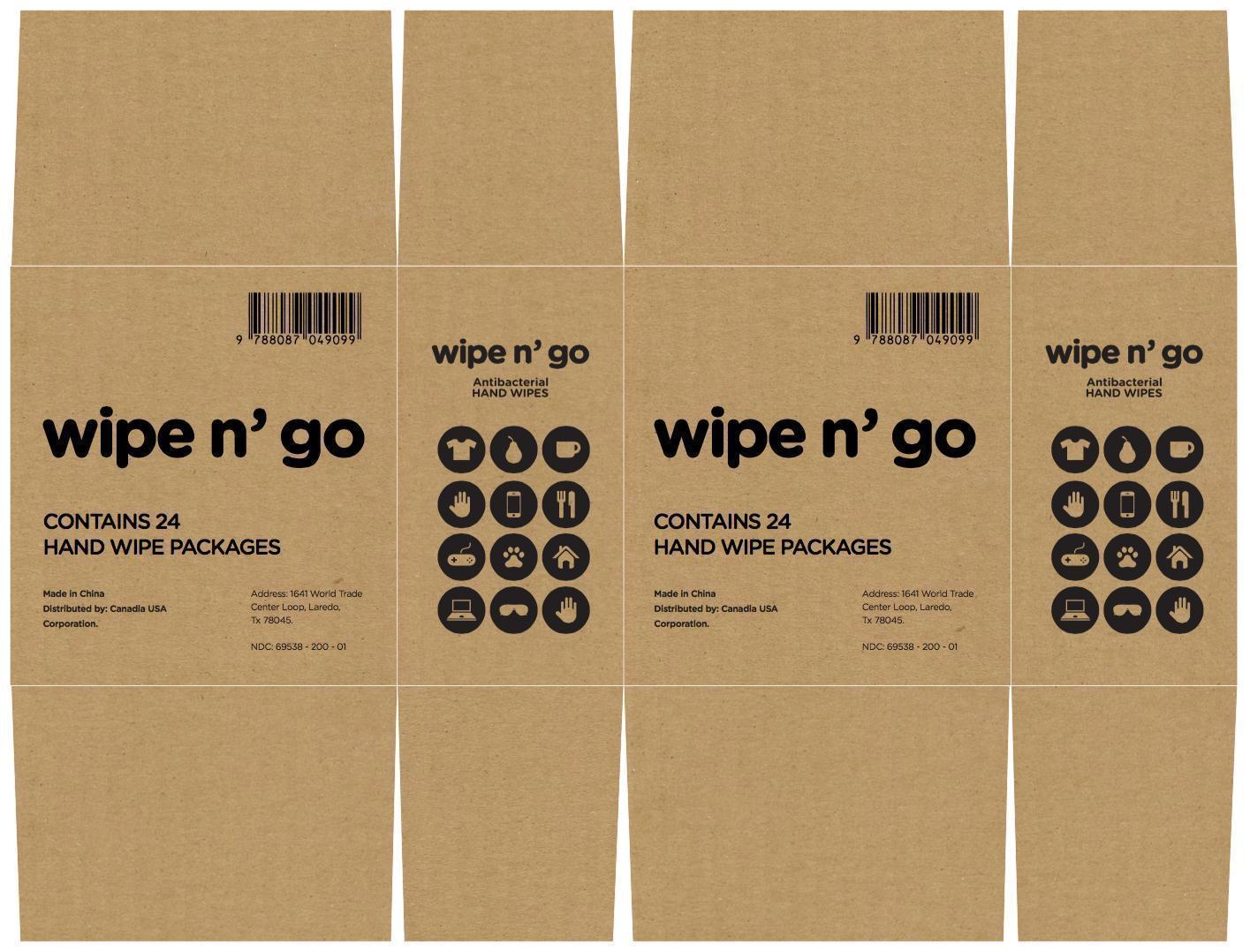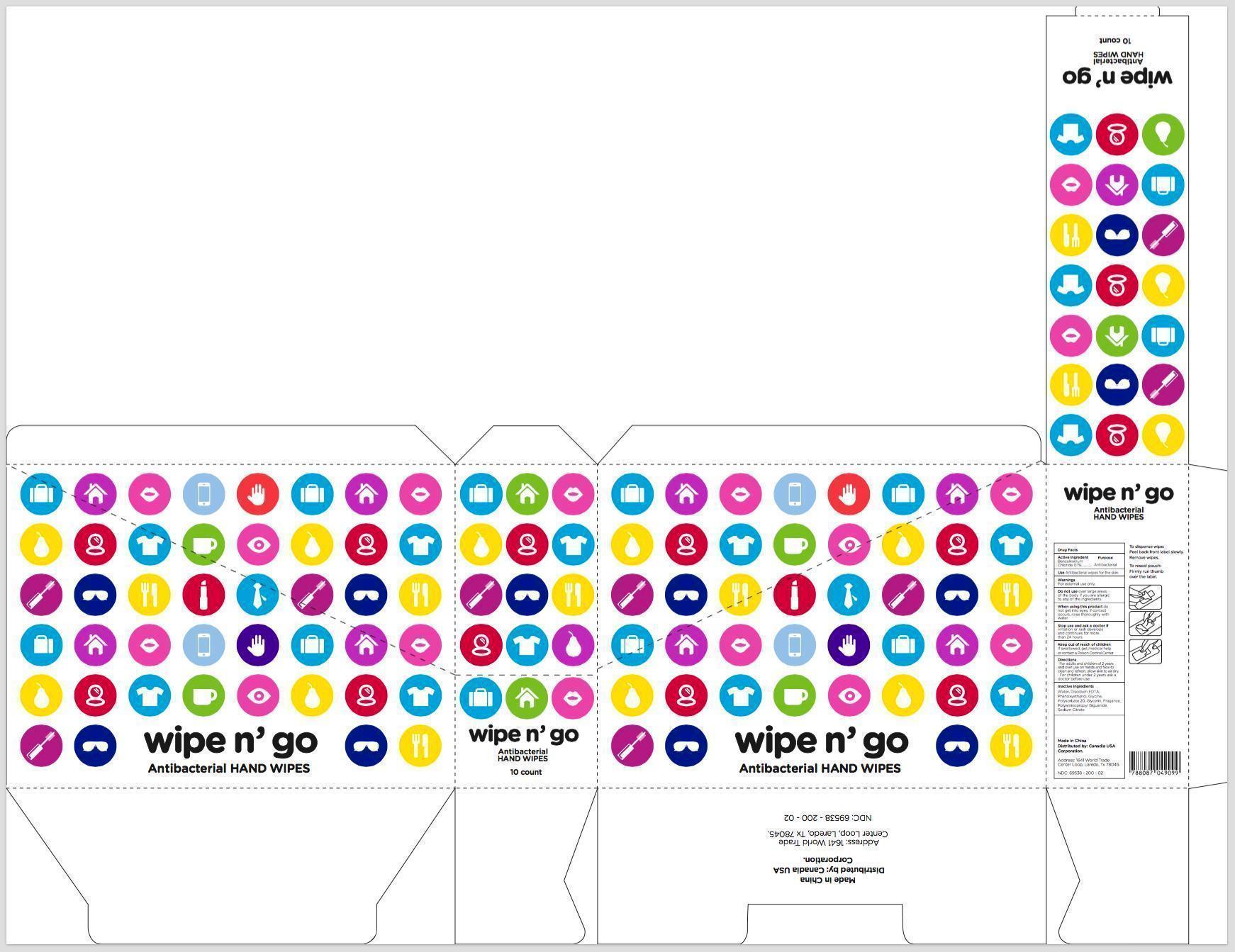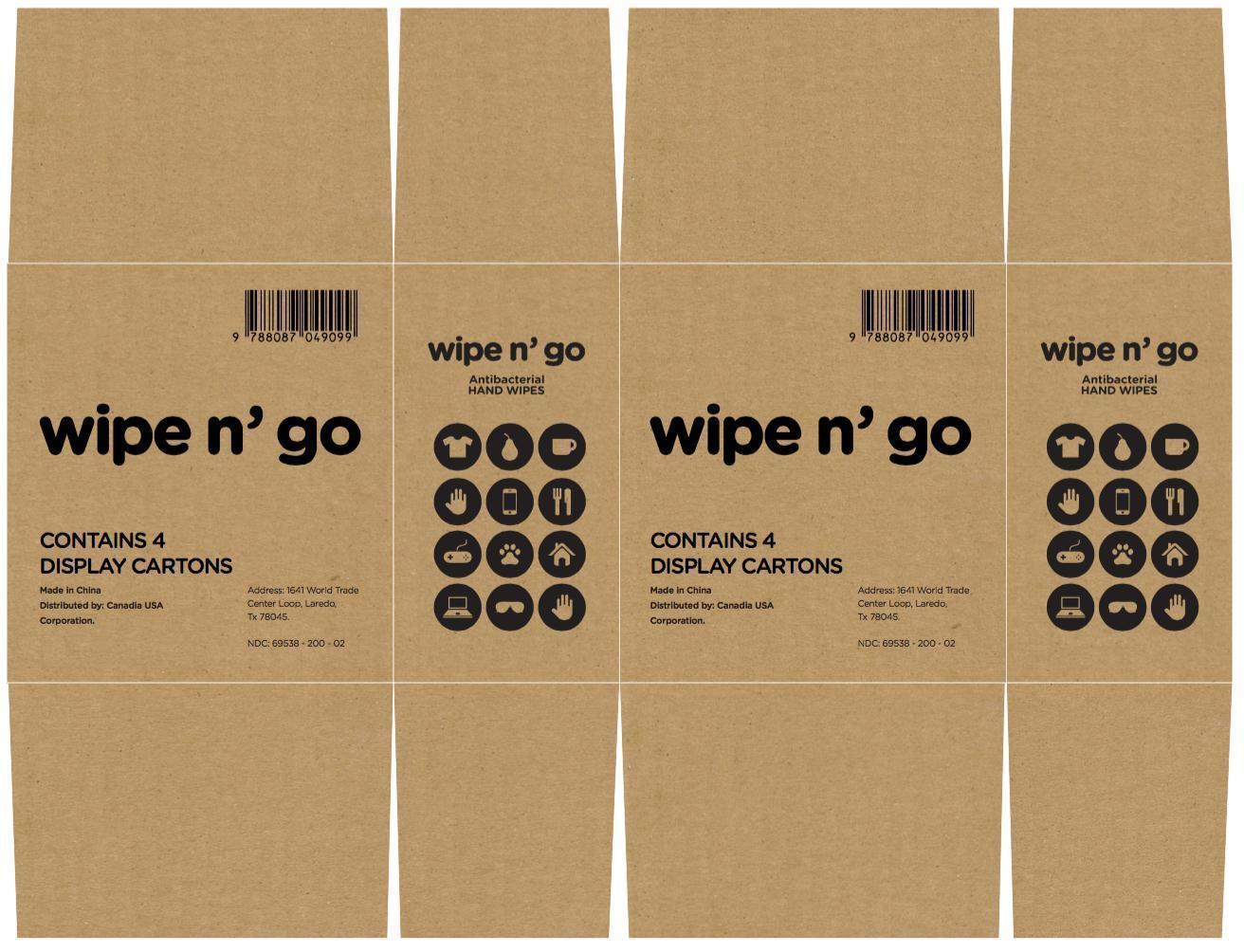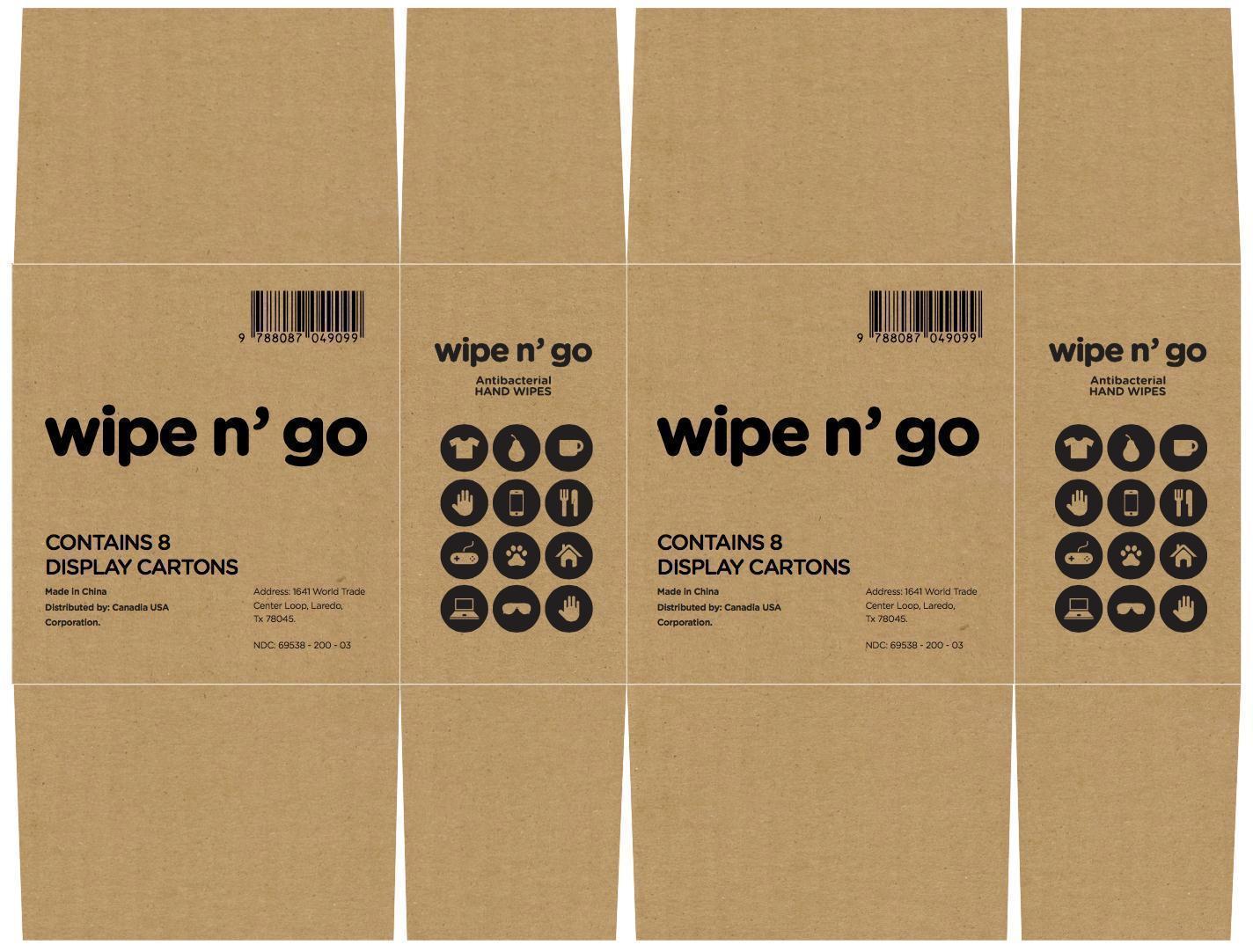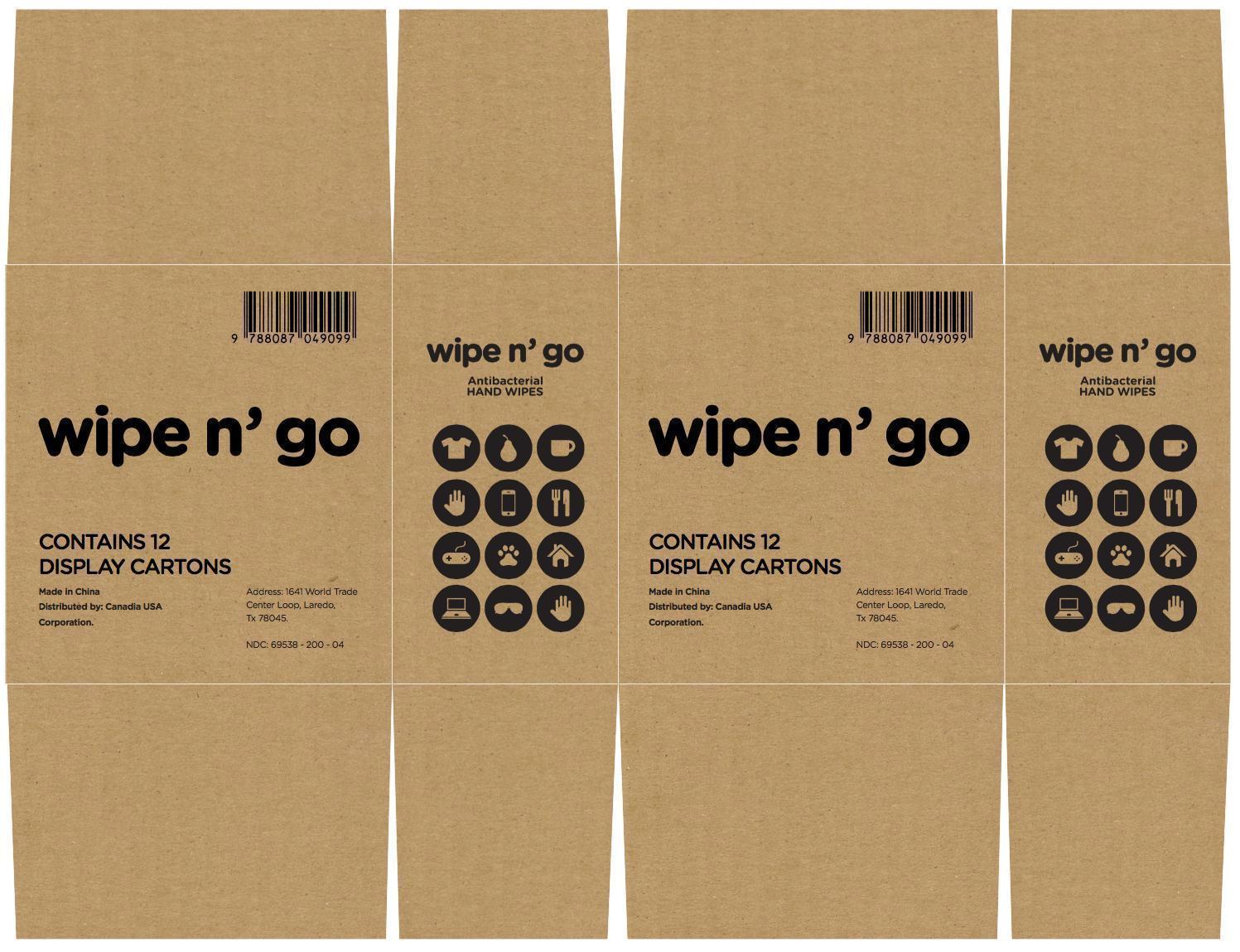 DRUG LABEL: Wipe n Go
NDC: 69538-200 | Form: SWAB
Manufacturer: CANADIA USA CORPORATION
Category: otc | Type: HUMAN OTC DRUG LABEL
Date: 20150824

ACTIVE INGREDIENTS: BENZALKONIUM CHLORIDE 0.13 g/100 g
INACTIVE INGREDIENTS: GLYCINE; WATER; EDETATE DISODIUM; PHENOXYETHANOL; POLYSORBATE 20; GLYCERIN; POLIHEXANIDE; SODIUM CITRATE

Drug Facts

Active ingredient

Benzalkonium Chloride, 0.1%

Purpose

Antibacterial

Uses

Antibacterial wipes for the skin.

Warnings

For external use only.

Do not use

over large areas of the body if you are allergic to any of the ingredients.

When using this product

do not get into eyes, if contact occurs, rinse thoroughly with water.

Stop use and ask a doctor if

irritation or rash develops and continues for more than 24 hours.

Keep out of reach of children

If swallowed, get medical help or contact a Poison Control Center right away.

Directions:

For adults and children of 2 years and over, use on hands and face to clean and refresh, allow skin to air dry.

For children under 2 years, ask a doctor before use.

Inactive ingredients:

Water, Disodium EDTA, Phenoxyethanol, Glycine, Polysorbate 20, Glycerin, Fragrance, Polyaminopropyl Biguanide, Sodium Citrate

Principal Display Panel

wipe n' go

Antibacterial HAND WIPES

Made in China

Distributed by: Canadia USA Corporation.